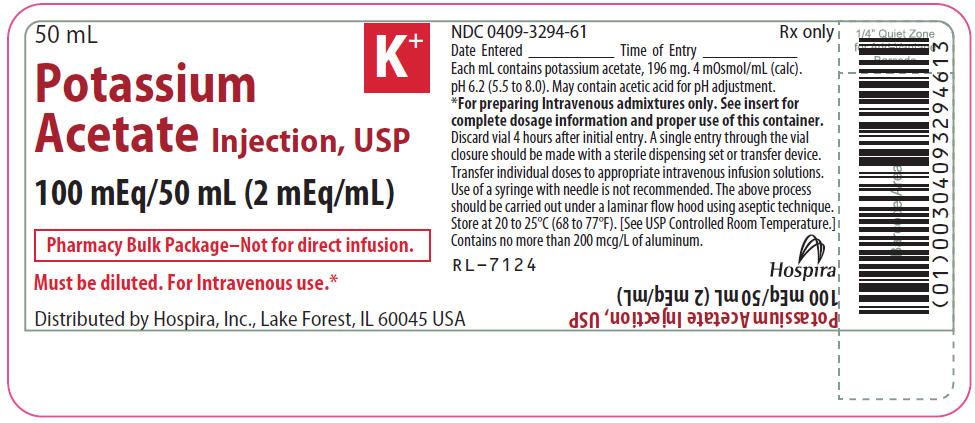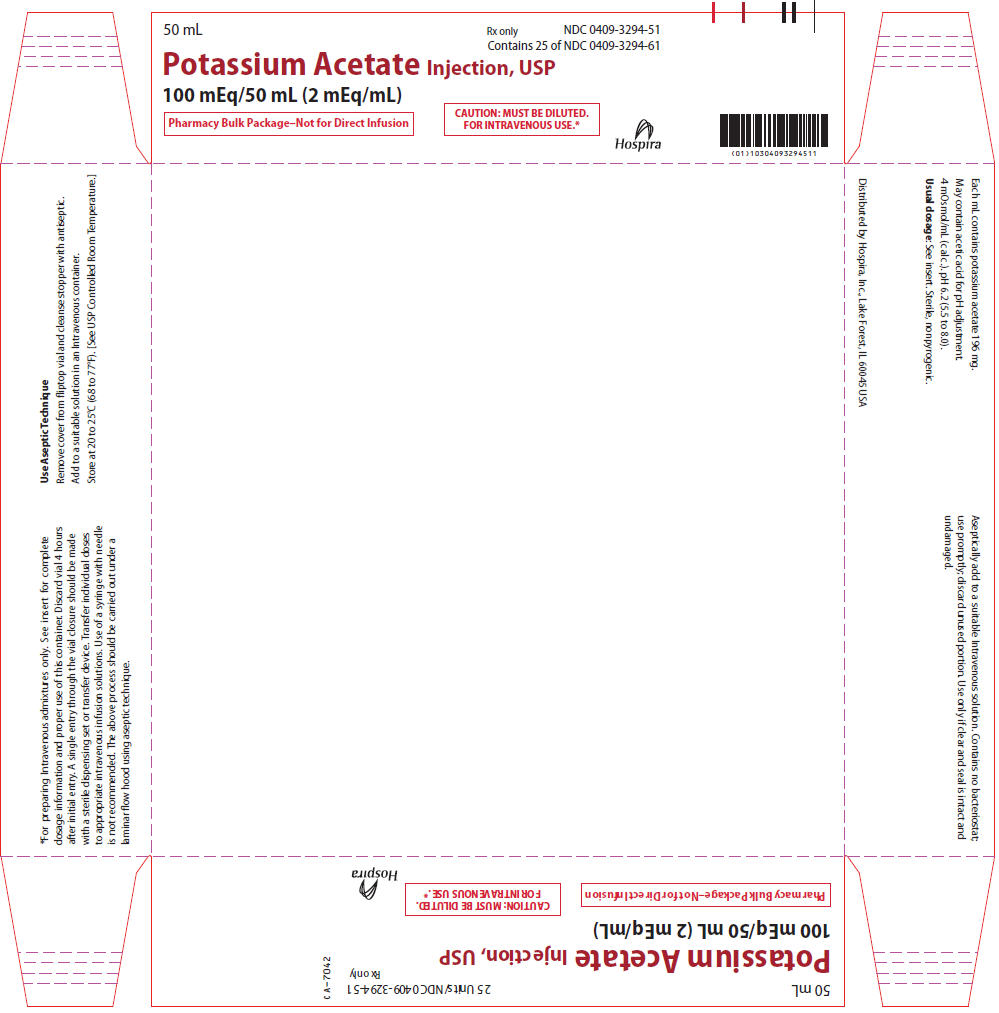 DRUG LABEL: Potassium Acetate
NDC: 0409-3294 | Form: INJECTION, SOLUTION, CONCENTRATE
Manufacturer: Hospira, Inc.
Category: prescription | Type: HUMAN PRESCRIPTION DRUG LABEL
Date: 20241115

ACTIVE INGREDIENTS: POTASSIUM ACETATE 196.3 mg/1 mL
INACTIVE INGREDIENTS: ACETIC ACID; WATER

Potassium Acetate
Injection, USP

100 mEq/50 mL

(2 mEq/mL)

(2 mEq K^+/mL and 2 mEq CH3COO^-/mL)

Pharmacy Bulk Package –

Not for Direct Infusion.

CONCENTRATED SOLUTION –

FOR INTRAVENOUS USE ONLY AFTER

DILUTION AND THOROUGH MIXING.

Glass Fliptop Vial

Rx only

DESCRIPTION

Potassium Acetate Injection, USP (2 mEq/mL) is a sterile, nonpyrogenic, concentrated solution of potassium acetate in water for injection. The solution is administered after dilution by the intravenous route as an electrolyte replenisher. It must not be administered undiluted.

Each mL contains 196 mg of potassium acetate which provides 2 mEq each of potassium (K^+) and acetate (CH3COO^-). The solution may contain acetic acid for pH adjustment. The pH is 6.2 (range: 5.5 to 8.0). The osmolar concentration is 4 mOsmol/mL (calc.); specific gravity is 1.089.

The Pharmacy Bulk Package is a sterile dosage which contains multiple single doses for use only in a pharmacy bulk admixture program.

The solution is intended as an alternative to potassium chloride to provide potassium ion (K^+) for addition to large volume infusion fluids for intravenous use.

Potassium Acetate, USP is chemically designated CH3COOK, and is comprised of colorless crystals or a white crystalline powder that is very soluble in water.

The Pharmacy Bulk Package is designed for use with manual, gravity flow operations and automated compounding devices for preparing sterile parenteral nutrient admixtures. The Pharmacy Bulk Package contains no bacteriostat, antimicrobial agent, or added buffer. Multiple single doses may be dispensed during continual aliquoting operations.

CLINICAL PHARMACOLOGY

As the principal cation of the intracellular fluid, potassium plays an important role in fluid and electrolyte balance. The normal potassium concentration in the intracellular fluid compartment is about 160 mEq/liter. The normal serum potassium range is 3.5 to 5.0 mEq/liter. The kidney normally regulates potassium balance but does not conserve potassium as well or as promptly as it conserves sodium. The daily turnover of potassium in the normal adult averages 50 to 150 mEq (milliequivalents) and represents 1.5 to 5% of the total potassium content of the body.

Acetate (CH3COO^-), a source of hydrogen ion acceptors, is an alternate source of bicarbonate (HCO3^-) by metabolic conversion in the liver. This has been shown to proceed readily, even in the presence of severe liver disease.

INDICATIONS AND USAGE

Potassium Acetate Injection, USP (2 mEq/mL) is indicated as a source of potassium, for the addition to large volume intravenous fluids, to prevent or correct hypokalemia in patients with restricted or no oral intake. It is also useful as an additive for preparing specific intravenous fluid formulas when the needs of the patient cannot be met by standard electrolyte or nutrient solutions.

CONTRAINDICATIONS

Potassium administration is contraindicated in patients with severe renal insufficiency or adrenal insufficiency and in diseases where high potassium levels may be encountered.

WARNINGS

Potassium Acetate Injection, USP (2 mEq/mL) must be diluted before use.

To avoid potassium intoxication, infuse potassium-containing solutions slowly. Potassium replacement therapy should be monitored whenever possible by continuous or serial electrocardiography (ECG). Serum potassium levels are not necessarily dependable indicators of tissue potassium levels.

Solutions which contain potassium ions should be used with great care, if at all, in patients with hyperkalemia, severe renal failure and in conditions in which potassium retention is present.

In patients with diminished renal function, administration of solutions containing potassium ions may result in potassium retention.

Solutions containing acetate ions should be used with great care in patients with metabolic or respiratory alkalosis. Acetate should be administered with great care in those conditions in which there is an increased level or an impaired utilization of this ion, such as severe hepatic insufficiency.

WARNING: This product contains aluminum that may be toxic. Aluminum may reach toxic levels with prolonged parenteral administration if kidney function is impaired. Premature neonates are particularly at risk because their kidneys are immature, and they require large amounts of calcium and phosphate solutions, which contain aluminum.

Research indicates that patients with impaired kidney function, including premature neonates, who receive parenteral levels of aluminum at greater than 4 to 5 mcg/kg/day accumulate aluminum at levels associated with central nervous system and bone toxicity. Tissue loading may occur at even lower rates of administration.

PRECAUTIONS

Do not administer unless solution is clear and seal is intact. Discard unused portion.

Potassium replacement therapy should be guided primarily by ECG monitoring and secondarily by the serum potassium level.

High plasma concentrations of potassium may cause death by cardiac depression, arrhythmias or arrest.

Use with caution in the presence of cardiac disease, particularly in digitalized patients or in the presence of renal disease.

Solutions containing acetate ion should be used with caution as excess administration may result in metabolic alkalosis.

Pregnancy

Animal reproduction studies have not been conducted with potassium acetate. It is also not known whether potassium acetate can cause fetal harm when administered to a pregnant woman or can affect reproduction capacity. Potassium acetate should be given to a pregnant woman only if clearly needed.

Pediatric Use: The safety and effectiveness of potassium acetate have been established in pediatric patients.

Geriatric Use: An evaluation of current literature revealed no clinical experience identifying differences in response between elderly and younger patients. In general, dose selection for an elderly patient should be cautious, usually starting at the low end of the dosing range, reflecting the greater frequency of decreased hepatic, renal, or cardiac function, and of concomitant disease or other drug therapy.

Potassium ions are known to be substantially excreted by the kidney, and the risk of toxic reactions may be greater in patients with impaired renal function. Because elderly patients are more likely to have decreased renal function, care should be taken in dose selection, and it may be useful to monitor renal function.

ADVERSE REACTIONS

Adverse reactions involve the possibility of potassium intoxication. The signs and symptoms of potassium intoxication include paresthesias of the extremities, flaccid paralysis, listlessness, mental confusion, weakness and heaviness of the legs, hypotension, cardiac arrhythmias, heart block, electrocardiographic abnormalities such as disappearance of P waves, spreading and slurring of the QRS complex with development of a biphasic curve and cardiac arrest. (See WARNINGS and PRECAUTIONS.)

OVERDOSAGE

In the event of overdosage, discontinue infusion containing potassium acetate immediately and institute corrective therapy as indicated to reduce elevated serum potassium levels and restore acid-base balance if necessary. (See WARNINGS, PRECAUTIONS, and ADVERSE REACTIONS.)

DOSAGE AND ADMINISTRATION

Potassium Acetate Injection, USP (2 mEq/mL) in the Pharmacy Bulk Package is designed for use with manual, gravity flow operations and automated compounding devices for preparing sterile nutrient admixtures.

Potassium Acetate Injection, USP (2 mEq/mL) is administered intravenously only after dilution in a larger volume of fluid. The dose and rate of administration are dependent upon the individual needs of the patient. ECG and serum potassium should be monitored as a guide to dosage. Using aseptic technique, all or part of the contents of one or more vials may be added to other intravenous fluids to provide any desired number of milliequivalents (mEq) of potassium (K^+) with an equal number of milliequivalents of acetate (CH3COO^-).

Maximum infusion rate: The infusion rate should not exceed 1 mEq/kg/hr.

Normal daily requirements:

Newborn: 2–6 mEq/kg/24 hr.

Children: 2–3 mEq/kg/24 hr.

Adult: 40 – 80 mEq/24 hr.

Intraosseous infusion can be an alternate route for drug administration when intravenous access is not readily available.

Parenteral drug products should be inspected visually for particulate matter and discoloration prior to administration, whenever solution and container permit. (See PRECAUTIONS.)

Directions for Dispensing From Pharmacy Bulk Package

The Pharmacy Bulk Package is for use in the Pharmacy Admixtures Service only. For hanger application, peel off the paper liner from both ends of the tape hanger to expose 3/4 inch long adhesive portions. Adhere each end to the label on the bottle. The vials should be suspended as a unit in the laminar flow hood.

A single entry through the vial closure should be made with a sterile dispensing set or transfer device. Transfer individual doses to appropriate intravenous infusion solutions. Use of a syringe with needle is not recommended as it may cause leakage and multiple entries will increase the potential of microbial and particulate contamination.

The above process should be carried out under a laminar flow hood using aseptic technique. Discard any unused portion within 4 hours after initial closure entry.

HOW SUPPLIED

Potassium Acetate Injection, USP is a Pharmacy Bulk Package which provides multiple single doses for continuous admixture compounding procedures is supplied as follows:

Unit of Sale | Concentration | Each
NDC 0409-3294-51 | 100 mEq/50 mL | NDC 0409-3294-61
Carton of 25 | (2 mEq/mL) | Glass Fliptop Vial

Store at 20 to 25°C (68 to 77°F). [See USP Controlled Room Temperature.]

Distributed by Hospira, Inc., Lake Forest, IL 60045 USA

LAB-0903-2.0

9/2017

PRINCIPAL DISPLAY PANEL - 50 mL Vial Label

50 mL

K^+

Potassium
Acetate Injection, USP

100 mEq/50 mL (2 mEq/mL)

Pharmacy Bulk Package–Not for direct infusion.

Must be diluted. For Intravenous use.*

Distributed by Hospira, Inc., Lake Forest, IL 60045 USA

PRINCIPAL DISPLAY PANEL - 50 mL Vial Tray

50 mL

Rx only
NDC 0409-3294-51
Contains 25 of NDC 0409-3294-61

Potassium Acetate Injection, USP
100 mEq/50 mL (2 mEq/mL)

Pharmacy Bulk Package–Not for Direct Infusion

CAUTION: MUST BE DILUTED.
FOR INTRAVENOUS USE.*

Hospira